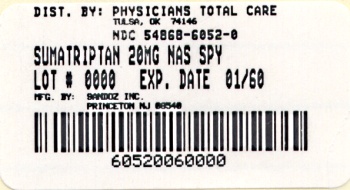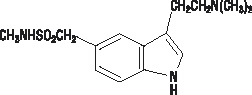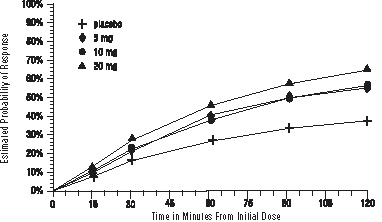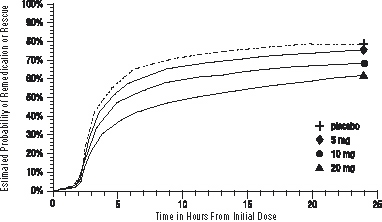 DRUG LABEL: SUMATRIPTAN
NDC: 54868-6052 | Form: SPRAY
Manufacturer: Physicians Total Care, Inc.
Category: prescription | Type: HUMAN PRESCRIPTION DRUG LABEL
Date: 20111212

ACTIVE INGREDIENTS: SUMATRIPTAN 20 mg/100 uL
INACTIVE INGREDIENTS: POTASSIUM PHOSPHATE, MONOBASIC; SODIUM PHOSPHATE, DIBASIC ANHYDROUS; SULFURIC ACID; SODIUM HYDROXIDE; WATER

Sumatriptan
Nasal Spray

DESCRIPTION

Sumatriptan Nasal Spray contains sumatriptan, a selective 5-hydroxytryptamine1 receptor subtype agonist. Sumatriptan is chemically designated as 3-[2-(dimethylamino)ethyl]-N-methyl-1H-indole-5-methanesulfonamide, and it has the following structure:

The empirical formula is C14H21N3O2S, representing a molecular weight of 295.4. Sumatriptan is a white to off-white powder that is readily soluble in water and in saline. Each Sumatriptan Nasal Spray contains 5 or 20 mg of sumatriptan in a 100-μL unit dose aqueous buffered solution containing monobasic potassium phosphate NF, anhydrous dibasic sodium phosphate USP, sulfuric acid NF, sodium hydroxide NF, and purified water USP. The pH of the solution is approximately 5.5. The osmolality of the solution is 372 or 742 mOsmol for the 5- and 20-mg Sumatriptan Nasal Spray, respectively.

CLINICAL PHARMACOLOGY

Mechanism of Action

Sumatriptan is an agonist for a vascular 5-hydroxytryptamine1 receptor subtype (probably a member of the 5-HT1D family) having only a weak affinity for 5-HT1A, 5-HT5A, and 5-HT7 receptors and no significant affinity (as measured using standard radioligand binding assays) or pharmacological activity at 5-HT2, 5-HT3, or 5-HT4 receptor subtypes or at alpha1-, alpha2-, or beta-adrenergic; dopamine1; dopamine2; muscarinic; or benzodiazepine receptors.

The vascular 5-HT1 receptor subtype that sumatriptan activates is present on cranial arteries in both dog and primate, on the human basilar artery, and in the vasculature of human dura mater and mediates vasoconstriction. This action in humans correlates with the relief of migraine headache. In addition to causing vasoconstriction, experimental data from animal studies show that sumatriptan also activates 5-HT1 receptors on peripheral terminals of the trigeminal nerve innervating cranial blood vessels. Such an action may contribute to the antimigrainous effect of sumatriptan in humans.

In the anesthetized dog, sumatriptan selectively reduces the carotid arterial blood flow with little or no effect on arterial blood pressure or total peripheral resistance. In the cat, sumatriptan selectively constricts the carotid arteriovenous anastomoses while having little effect on blood flow or resistance in cerebral or extracerebral tissues.

Pharmacokinetics

In a study of 20 female volunteers, the mean maximum concentration following a 5- and 20-mg intranasal dose was 5 and 16 ng/mL, respectively. The mean Cmax following a 6-mg subcutaneous injection is 71 ng/mL (range: 49 to 110 ng/mL). The mean Cmax is 18 ng/mL (range: 7 to 47 ng/mL) following oral dosing with 25 mg and 51 ng/mL (range: 28 to 100 ng/mL) following oral dosing with 100 mg of sumatriptan. In a study of 24 male volunteers, the bioavailability relative to subcutaneous injection was low, approximately 17%, primarily due to presystemic metabolism and partly due to incomplete absorption.

Protein binding, determined by equilibrium dialysis over the concentration range of 10 to 1,000 ng/mL, is low, approximately 14% to 21%. The effect of sumatriptan on the protein binding of other drugs has not been evaluated, but would be expected to be minor, given the low rate of protein binding. The mean volume of distribution after subcutaneous dosing is 2.7 L/kg and the total plasma clearance is approximately 1,200 mL/min.

The elimination half-life of sumatriptan administered as a nasal spray is approximately 2 hours, similar to the half-life seen after subcutaneous injection. Only 3% of the dose is excreted in the urine as unchanged sumatriptan; 42% of the dose is excreted as the major metabolite, the indole acetic acid analogue of sumatriptan.

Clinical and pharmacokinetic data indicate that administration of two 5-mg doses, 1 dose in each nostril, is equivalent to administration of a single 10-mg dose in 1 nostril.

Special Populations

Renal Impairment: The effect of renal impairment on the pharmacokinetics of sumatriptan has not been examined, but little clinical effect would be expected as sumatriptan is largely metabolized to an inactive substance.

Hepatic Impairment: The effect of hepatic disease on the pharmacokinetics of subcutaneously and orally administered sumatriptan has been evaluated, but the intranasal dosage form has not been studied in hepatic impairment. There were no statistically significant differences in the pharmacokinetics of subcutaneously administered sumatriptan in hepatically impaired patients compared with healthy controls. However, the liver plays an important role in the presystemic clearance of orally administered sumatriptan. In 1 small study involving oral sumatriptan in hepatically impaired patients (N = 8) matched for sex, age, and weight with healthy subjects, the hepatically impaired patients had an approximately 70% increase in AUC and Cmax and a Tmax 40 minutes earlier compared with the healthy subjects. The bioavailability of nasally absorbed sumatriptan following intranasal administration, which would not undergo first-pass metabolism, should not be altered in hepatically impaired patients. The bioavailability of the swallowed portion of the intranasal sumatriptan dose has not been determined, but would be increased in these patients. The swallowed intranasal dose is small, however, compared with the usual oral dose, so that its impact should be minimal.

Age: The pharmacokinetics of oral sumatriptan in the elderly (mean age: 72 years; 2 males and 4 females) and in patients with migraine (mean age: 38 years; 25 males and 155 females) were similar to that in healthy male subjects (mean age: 30 years). Intranasal sumatriptan has not been evaluated for age differences (see PRECAUTIONS: Geriatric Use).

Race: The systemic clearance and Cmax of sumatriptan were similar in black (n = 34) and Caucasian (n = 38) healthy male subjects. Intranasal sumatriptan has not been evaluated for race differences.

Drug Interactions

Monoamine Oxidase Inhibitors: Treatment with monoamine oxidase inhibitors (MAOIs) generally leads to an increase of sumatriptan plasma levels (see CONTRAINDICATIONS and PRECAUTIONS).

MAOI interaction studies have not been performed with intranasal sumatriptan. Due to gut and hepatic metabolic first-pass effects, the increase of systemic exposure after coadministration of an MAO-A inhibitor with oral sumatriptan is greater than after coadministration of the MAOI with subcutaneous sumatriptan. The effects of an MAOI on systemic exposure after intranasal sumatriptan would be expected to be greater than the effect after subcutaneous sumatriptan but smaller than the effect after oral sumatriptan because only swallowed drug would be subject to first-pass effects.

In a study of 14 healthy females, pretreatment with an MAO-A inhibitor decreased the clearance of subcutaneous sumatriptan. Under the conditions of this experiment, the result was a 2-fold increase in the area under the sumatriptan plasma concentration x time curve (AUC), corresponding to a 40% increase in elimination half-life. This interaction was not evident with an MAO-B inhibitor.

A small study evaluating the effect of pretreatment with an MAO-A inhibitor on the bioavailability from a 25-mg oral sumatriptan tablet resulted in an approximately 7-fold increase in systemic exposure.

Xylometazoline: An in vivo drug interaction study indicated that 3 drops of xylometazoline (0.1% w/v), a decongestant, administered 15 minutes prior to a 20-mg nasal dose of sumatriptan did not alter the pharmacokinetics of sumatriptan.

CLINICAL TRIALS

The efficacy of sumatriptan nasal spray in the acute treatment of migraine headaches was demonstrated in 8, randomized, double-blind, placebo-controlled studies, of which 5 used the recommended dosing regimen and used the marketed formulation. Patients enrolled in these 5 studies were predominately female (86%) and Caucasian (95%), with a mean age of 41 (range of 18 to 65). Patients were instructed to treat a moderate to severe headache. Headache response, defined as a reduction in headache severity from moderate or severe pain to mild or no pain, was assessed up to 2 hours after dosing. Associated symptoms such as nausea, photophobia, and phonophobia were also assessed. Maintenance of response was assessed for up to 24 hours postdose. A second dose of sumatriptan nasal spray or other medication was allowed 2 to 24 hours after the initial treatment for recurrent headache. The frequency and time to use of these additional treatments were also determined. In all studies, doses of 10 and 20 mg were compared with placebo in the treatment of 1 to 3 migraine attacks. Patients received doses as a single spray into 1 nostril. In 2 studies, a 5-mg dose was also evaluated.

In all 5 trials utilizing the market formulation and recommended dosage regimen, the percentage of patients achieving headache response 2 hours after treatment was significantly greater among patients receiving sumatriptan nasal spray at all doses (with one exception) compared with those who received placebo. In 4 of the 5 studies, there was a statistically significant greater percentage of patients with headache response at 2 hours in the 20-mg group when compared with the lower dose groups (5 and 10 mg). There were no statistically significant differences between the 5- and 10-mg dose groups in any study. The results from the 5 controlled clinical trials are summarized in Table 1. Note that, in general, comparisons of results obtained in studies conducted under different conditions by different investigators with different samples of patients are ordinarily unreliable for purposes of quantitative comparison.

Table 1. Percentage of Patients With Headache Response (No or Mild Pain) 2 Hours Following Treatment
 | Placebo | Sumatriptan Nasal Spray; 5 mg | Sumatriptan Nasal Spray; 10 mg | Sumatriptan Nasal Spray; 20 mg
Study 1 | 25% | 49%a | 46%a | 64%abc
 | (n = 63) | (n = 121) | (n = 112) | (n = 118)
Study 2 | 25% | Not applicable | 44%a | 55%ab
 | (n = 138) |  | (n = 273) | (n = 277)
Study 3 | 35% | Not applicable | 54%a | 63%a
 | (n = 100) |  | (n = 106) | (n = 202)
Study 4 | 29% | Not applicable | 43% | 62%ab
 | (n = 112) |  | (n = 106) | (n = 215)
Study 5d | 36% | 45%a | 53%a | 60%ac
 | (n = 198) | (n = 296) | (n = 291) | (n = 286)

ap<0.05 in comparison with placebo.

bp<0.05 in comparison with 10 mg.

cp<0.05 in comparison with 5 mg.

dData are for attack 1 only of multiattack study for comparison.

The estimated probability of achieving an initial headache response over the 2 hours following treatment is depicted in Figure 1.

Figure 1. Estimated Probability of Achieving Initial Headache Response Within 120 Minutesa

aThe figure shows the probability over time of obtaining headache response (no or mild pain) following treatment with intranasal sumatriptan. The averages displayed are based on pooled data from the 5 clinical controlled trials providing evidence of efficacy. Kaplan-Meier plot with patients not achieving response within 120 minutes censored to 120 minutes.

For patients with migraine-associated nausea, photophobia, and phonophobia at baseline, there was a lower incidence of these symptoms at 2 hours following administration of sumatriptan nasal spray compared with placebo.

Two to 24 hours following the initial dose of study treatment, patients were allowed to use additional treatment for pain relief in the form of a second dose of study treatment or other medication. The estimated probability of patients taking a second dose or other medication for migraine over the 24 hours following the initial dose of study treatment is summarized in Figure 2.

Figure 2. The Estimated Probability of Patients Taking a Second Dose or Other Medication for Migraine Over the 24 Hours Following the Initial Dose of Study Treatmenta

aKaplan-Meier plot based on data obtained in the 3 clinical controlled trials providing evidence of efficacy with patients not using additional treatments censored to 24 hours. Plot also includes patients who had no response to the initial dose. No remedication was allowed within 2 hours postdose.

There is evidence that doses above 20 mg do not provide a greater effect than 20 mg. There was no evidence to suggest that treatment with sumatriptan was associated with an increase in the severity of recurrent headaches. The efficacy of sumatriptan nasal spray was unaffected by presence of aura; duration of headache prior to treatment; gender, age, or weight of the patient; or concomitant use of common migraine prophylactic drugs (e.g., beta-blockers, calcium channel blockers, tricyclic antidepressants). There were insufficient data to assess the impact of race on efficacy.

INDICATIONS AND USAGE

Sumatriptan Nasal Spray is indicated for the acute treatment of migraine attacks with or without aura in adults.

Sumatriptan Nasal Spray is not intended for the prophylactic therapy of migraine or for use in the management of hemiplegic or basilar migraine (see CONTRAINDICATIONS). Safety and effectiveness of sumatriptan nasal spray have not been established for cluster headache, which is present in an older, predominantly male population.

CONTRAINDICATIONS

Sumatriptan Nasal Spray should not be given to patients with history, symptoms, or signs of ischemic cardiac, cerebrovascular, or peripheral vascular syndromes. In addition, patients with other significant underlying cardiovascular diseases should not receive Sumatriptan Nasal Spray. Ischemic cardiac syndromes include, but are not limited to, angina pectoris of any type (e.g., stable angina of effort, vasospastic forms of angina such as the Prinzmetal variant), all forms of myocardial infarction, and silent myocardial ischemia. Cerebrovascular syndromes include, but are not limited to, strokes of any type as well as transient ischemic attacks. Peripheral vascular disease includes, but is not limited to, ischemic bowel disease (see WARNINGS).

Because Sumatriptan Nasal Spray may increase blood pressure, it should not be given to patients with uncontrolled hypertension.

Concurrent administration of MAO-A inhibitors or use within 2 weeks of discontinuation of MAO-A inhibitor therapy is contraindicated (see CLINICAL PHARMACOLOGY: Drug Interactions and PRECAUTIONS: Drug Interactions).

Sumatriptan Nasal Spray and any ergotamine-containing or ergot-type medication (like dihydroergotamine or methysergide) should not be used within 24 hours of each other, nor should Sumatriptan Nasal Spray and another 5-HT1 agonist.

Sumatriptan Nasal Spray should not be administered to patients with hemiplegic or basilar migraine.

Sumatriptan Nasal Spray is contraindicated in patients with hypersensitivity to sumatriptan or any of its components.

Sumatriptan Nasal Spray is contraindicated in patients with severe hepatic impairment.

WARNINGS

Sumatriptan Nasal Spray should only be used where a clear diagnosis of migraine headache has been established.

Risk of Myocardial Ischemia and/or Infarction and Other Adverse Cardiac Events

Sumatriptan should not be given to patients with documented ischemic or vasospastic coronary artery disease (CAD) (see CONTRAINDICATIONS). It is strongly recommended that sumatriptan not be given to patients in whom unrecognized CAD is predicted by the presence of risk factors (e.g., hypertension, hypercholesterolemia, smoker, obesity, diabetes, strong family history of CAD, female with surgical or physiological menopause, male over 40 years of age) unless a cardiovascular evaluation provides satisfactory clinical evidence that the patient is reasonably free of coronary artery and ischemic myocardial disease or other significant underlying cardiovascular disease. The sensitivity of cardiac diagnostic procedures to detect cardiovascular disease or predisposition to coronary artery vasospasm is modest, at best. If, during the cardiovascular evaluation, the patient’s medical history or electrocardiographic investigations reveal findings indicative of, or consistent with, coronary artery vasospasm or myocardial ischemia, sumatriptan should not be administered (see CONTRAINDICATIONS).

For patients with risk factors predictive of CAD, who are determined to have a satisfactory cardiovascular evaluation, it is strongly recommended that administration of the first dose of Sumatriptan Nasal Spray take place in the setting of a physician’s office or similar medically staffed and equipped facility unless the patient has previously received sumatriptan. Because cardiac ischemia can occur in the absence of clinical symptoms, consideration should be given to obtaining an electrocardiogram (ECG) during the interval immediately following the first dose in these patients with risk factors.

It is recommended that patients who are intermittent long-term users of sumatriptan and who have or acquire risk factors predictive of CAD, as described above, undergo periodic interval cardiovascular evaluation as they continue to use sumatriptan.

The systematic approach described above is intended to reduce the likelihood that patients with unrecognized cardiovascular disease will be inadvertently exposed to sumatriptan.

Drug-Associated Cardiac Events and Fatalities

Serious adverse cardiac events, including acute myocardial infarction, life-threatening disturbances of cardiac rhythm, and death have been reported within a few hours following the administration of sumatriptan injection or tablets. Considering the extent of use of sumatriptan in patients with migraine, the incidence of these events is extremely low.

The fact that sumatriptan can cause coronary vasospasm, that some of these events have occurred in patients with no prior cardiac disease history and with documented absence of CAD, and the close proximity of the events to sumatriptan use support the conclusion that some of these cases were caused by the drug. In many cases, however, where there has been known underlying coronary artery disease, the relationship is uncertain.

Premarketing Experience With Sumatriptan: Among approximately 4,000 patients with migraine who participated in premarketing controlled and uncontrolled clinical trials of sumatriptan nasal spray, 1 patient experienced an asymptomatic subendocardial infarction possibly subsequent to a coronary vasospastic event.

Of 6,348 patients with migraine who participated in premarketing controlled and uncontrolled clinical trials of oral sumatriptan, 2 experienced clinical adverse events shortly after receiving oral sumatriptan that may have reflected coronary vasospasm. Neither of these adverse events was associated with a serious clinical outcome.

Among the more than 1,900 patients with migraine who participated in premarketing controlled clinical trials of subcutaneous sumatriptan, there were 8 patients who sustained clinical events during or shortly after receiving sumatriptan that may have reflected coronary artery vasospasm. Six of these 8 patients had ECG changes consistent with transient ischemia, but without accompanying clinical symptoms or signs. Of these 8 patients, 4 had either findings suggestive of CAD or risk factors predictive of CAD prior to study enrollment.

Postmarketing Experience With Sumatriptan: Serious cardiovascular events, some resulting in death, have been reported in association with the use of sumatriptan injection or tablets. The uncontrolled nature of postmarketing surveillance, however, makes it impossible to determine definitively the proportion of the reported cases that were actually caused by sumatriptan or to reliably assess causation in individual cases. On clinical grounds, the longer the latency between the administration of sumatriptan and the onset of the clinical event, the less likely the association is to be causative. Accordingly, interest has focused on events beginning within 1 hour of the administration of sumatriptan.

Cardiac events that have been observed to have onset within 1 hour of sumatriptan administration include: coronary artery vasospasm, transient ischemia, myocardial infarction, ventricular tachycardia and ventricular fibrillation, cardiac arrest, and death.

Some of these events occurred in patients who had no findings of CAD and appear to represent consequences of coronary artery vasospasm. However, among domestic reports of serious cardiac events within 1 hour of sumatriptan administration, almost all of the patients had risk factors predictive of CAD and the presence of significant underlying CAD was established in most cases (see CONTRAINDICATIONS).

Drug-Associated Cerebrovascular Events and Fatalities

Cerebral hemorrhage, subarachnoid hemorrhage, stroke, and other cerebrovascular events have been reported in patients treated with oral or subcutaneous sumatriptan, and some have resulted in fatalities. The relationship of sumatriptan to these events is uncertain. In a number of cases, it appears possible that the cerebrovascular events were primary, sumatriptan having been administered in the incorrect belief that the symptoms experienced were a consequence of migraine when they were not. As with other acute migraine therapies, before treating headaches in patients not previously diagnosed as migraineurs, and in migraineurs who present with atypical symptoms, care should be taken to exclude other potentially serious neurological conditions. It should also be noted that patients with migraine may be at increased risk of certain cerebrovascular events (e.g., cerebrovascular accident, transient ischemic attack).

Other Vasospasm-Related Events

Sumatriptan may cause vasospastic reactions other than coronary artery vasospasm. Both peripheral vascular ischemia and colonic ischemia with abdominal pain and bloody diarrhea have been reported. Very rare reports of transient and permanent blindness and significant partial vision loss have been reported with the use of sumatriptan. Visual disorders may also be part of a migraine attack.

Serotonin Syndrome

The development of a potentially life-threatening serotonin syndrome may occur with triptans, including treatment with sumatriptan, particularly during combined use with selective serotonin reuptake inhibitors (SSRIs) or serotonin norepinephrine reuptake inhibitors (SNRIs). If concomitant treatment with sumatriptan and an SSRI (e.g., fluoxetine, paroxetine, sertraline, fluvoxamine, citalopram, escitalopram) or SNRI (e.g., venlafaxine, duloxetine) is clinically warranted, careful observation of the patient is advised, particularly during treatment initiation and dose increases. Serotonin syndrome symptoms may include mental status changes (e.g., agitation, hallucinations, coma), autonomic instability (e.g., tachycardia, labile blood pressure, hyperthermia), neuromuscular aberrations (e.g., hyperreflexia, incoordination), and/or gastrointestinal symptoms (e.g., nausea, vomiting, diarrhea).

Increase in Blood Pressure

Significant elevation in blood pressure, including hypertensive crisis, has been reported on rare occasions in patients with and without a history of hypertension. Sumatriptan is contraindicated in patients with uncontrolled hypertension (see CONTRAINDICATIONS). Sumatriptan should be administered with caution to patients with controlled hypertension as transient increases in blood pressure and peripheral vascular resistance have been observed in a small proportion of patients.

Local Irritation

Of the 3,378 patients using the nasal spray (5-, 10-, or 20-mg doses) on 1 or 2 occasions in controlled clinical studies, approximately 5% noted irritation in the nose and throat. Irritative symptoms such as burning, numbness, paresthesia, discharge, and pain or soreness were noted to be severe in about 1% of patients treated. The symptoms were transient and in approximately 60% of the cases, the symptoms resolved in less than 2 hours. Limited examinations of the nose and throat did not reveal any clinically noticeable injury in these patients.

The consequences of extended and repeated use of sumatriptan nasal spray on the nasal and/or respiratory mucosa have not been systematically evaluated in patients. No increase in the incidence of local irritation was observed in patients using sumatriptan nasal spray repeatedly for up to 1 year.

In inhalation studies in rats dosed daily for up to 1 month at exposures as low as one half the maximum daily human exposure (based on dose per surface area of nasal cavity), epithelial hyperplasia (with and without keratinization) and squamous metaplasia were observed in the larynx at all doses tested. These changes were partially reversible after a 2-week drug-free period. When dogs were dosed daily with various formulations by intranasal instillation for up to 13 weeks at exposures of 2 to 4 times the maximum daily human exposure (based on dose per surface area of nasal cavity), respiratory and nasal mucosa exhibited evidence of epithelial hyperplasia, focal squamous metaplasia, granulomata, bronchitis, and fibrosing alveolitis. A no-effect dose was not established. The changes observed in both species are not considered to be signs of either preneoplastic or neoplastic transformation.

Local effects on nasal and respiratory tissues after chronic intranasal dosing in animals have not been studied.

Concomitant Drug Use

In patients taking MAO-A inhibitors, sumatriptan plasma levels attained after treatment with recommended doses are 2-fold (following subcutaneous administration) to 7-fold (following oral administration) higher than those obtained under other conditions. Accordingly, the coadministration of sumatriptan and an MAO-A inhibitor is contraindicated (see CLINICAL PHARMACOLOGY and CONTRAINDICATIONS).

Hypersensitivity

Hypersensitivity (anaphylaxis/anaphylactoid) reactions have occurred on rare occasions in patients receiving sumatriptan. Such reactions can be life threatening or fatal. In general, hypersensitivity reactions to drugs are more likely to occur in individuals with a history of sensitivity to multiple allergens (see CONTRAINDICATIONS).

PRECAUTIONS

General

Chest discomfort and jaw or neck tightness have been reported infrequently following the administration of sumatriptan nasal spray and have also been reported following use of sumatriptan tablets. Chest, jaw, or neck tightness is relatively common after administration of sumatriptan injection. Only rarely have these symptoms been associated with ischemic ECG changes. However, because sumatriptan may cause coronary artery vasospasm, patients who experience signs or symptoms suggestive of angina following sumatriptan should be evaluated for the presence of CAD or a predisposition to Prinzmetal variant angina before receiving additional doses of sumatriptan, and should be monitored electrocardiographically if dosing is resumed and similar symptoms recur. Similarly, patients who experience other symptoms or signs suggestive of decreased arterial flow, such as ischemic bowel syndrome or Raynaud syndrome following sumatriptan should be evaluated for atherosclerosis or predisposition to vasospasm (see WARNINGS).

Sumatriptan should also be administered with caution to patients with diseases that may alter the absorption, metabolism, or excretion of drugs, such as impaired hepatic or renal function.

There have been rare reports of seizure following administration of sumatriptan. Sumatriptan should be used with caution in patients with a history of epilepsy or conditions associated with a lowered seizure threshold.

Care should be taken to exclude other potentially serious neurologic conditions before treating headache in patients not previously diagnosed with migraine headache or who experience a headache that is atypical for them. There have been rare reports where patients received sumatriptan for severe headaches that were subsequently shown to have been secondary to an evolving neurologic lesion (see WARNINGS).

For a given attack, if a patient does not respond to the first dose of sumatriptan, the diagnosis of migraine headache should be reconsidered before administration of a second dose.

Overuse of acute migraine treatments has been associated with the exacerbation of headache (medication overuse headache) in susceptible patients. Withdrawal of the treatment may be necessary.

Binding to Melanin-Containing Tissues

In rats treated with a single subcutaneous dose (0.5 mg/kg) or oral dose (2 mg/kg) of radiolabeled sumatriptan, the elimination half-life of radioactivity from the eye was 15 and 23 days, respectively, suggesting that sumatriptan and/or its metabolites bind to the melanin of the eye. Comparable studies were not performed by the intranasal route. Because there could be an accumulation in melanin-rich tissues over time, this raises the possibility that sumatriptan could cause toxicity in these tissues after extended use. However, no effects on the retina related to treatment with sumatriptan were noted in any of the oral or subcutaneous toxicity studies. Although no systematic monitoring of ophthalmologic function was undertaken in clinical trials, and no specific recommendations for ophthalmologic monitoring are offered, prescribers should be aware of the possibility of long-term ophthalmologic effects.

Corneal Opacities

Sumatriptan causes corneal opacities and defects in the corneal epithelium in dogs; this raises the possibility that these changes may occur in humans. While patients were not systematically evaluated for these changes in clinical trials, and no specific recommendations for monitoring are being offered, prescribers should be aware of the possibility of these changes (see ANIMAL TOXICOLOGY).

Information for Patients

See PATIENT INFORMATION at the end of this labeling for the text of the separate leaflet provided for patients.

Patients should be cautioned about the risk of serotonin syndrome with the use of sumatriptan or other triptans, especially during combined use with SSRIs or SNRIs.

Laboratory Tests

No specific laboratory tests are recommended for monitoring patients prior to and/or after treatment with sumatriptan.

Drug Interactions

Selective Serotonin Reuptake Inhibitors/Serotonin Norepinephrine Reuptake Inhibitors and Serotonin Syndrome: Cases of life-threatening serotonin syndrome have been reported during combined use of SSRIs or SNRIs and triptans (see WARNINGS).

Ergot-Containing Drugs: Ergot-containing drugs have been reported to cause prolonged vasospastic reactions. Because there is a theoretical basis that these effects may be additive, use of ergotamine-containing or ergot-type medications (like dihydroergotamine or methysergide) and sumatriptan within 24 hours of each other should be avoided (see CONTRAINDICATIONS).

Monoamine Oxidase-A Inhibitors: MAO-A inhibitors reduce sumatriptan clearance, significantly increasing systemic exposure. Therefore, the use of Sumatriptan Nasal Spray in patients receiving MAO-A inhibitors is contraindicated (see CLINICAL PHARMACOLOGY and CONTRAINDICATIONS).

Drug/Laboratory Test Interactions

Sumatriptan is not known to interfere with commonly employed clinical laboratory tests.

Carcinogenesis, Mutagenesis, Impairment of Fertility

Carcinogenesis: In carcinogenicity studies, rats and mice were given sumatriptan by oral gavage (rats; 104 weeks) or drinking water (mice; 78 weeks). Average exposures achieved in mice receiving the highest dose (target dose of 160 mg/kg/day) were approximately 184 times the exposure attained in humans after the maximum recommended single intranasal dose of 20 mg. The highest dose administered to rats (160 mg/kg/day, reduced from 360 mg/kg/day during week 21) was approximately 78 times the maximum recommended single intranasal dose of 20 mg on a mg/m^2 basis. There was no evidence of an increase in tumors in either species related to sumatriptan administration. Local effects on nasal and respiratory tissue after chronic intranasal dosing in animals have not been evaluated (see WARNINGS).

Mutagenesis: Sumatriptan was not mutagenic in the presence or absence of metabolic activation when tested in 2 gene mutation assays (the Ames test and the in vitro mammalian Chinese hamster V79/HGPRT assay). In 2 cytogenetics assays (the in vitro human lymphocyte assay and the in vivo rat micronucleus assay) sumatriptan was not associated with clastogenic activity.

Impairment of Fertility: In a study in which male and female rats were dosed daily with oral sumatriptan prior to and throughout the mating period, there was a treatment-related decrease in fertility secondary to a decrease in mating in animals treated with 50 and 500 mg/kg/day. The highest no-effect dose for this finding was 5 mg/kg/day, or approximately twice the maximum recommended single human intranasal dose of 20 mg on a mg/m^2 basis. It is not clear whether the problem is associated with treatment of the males or females or both combined. In a similar study by the subcutaneous route there was no evidence of impaired fertility at 60 mg/kg/day, the maximum dose tested, which is equivalent to approximately 29 times the maximum recommended single human intranasal dose of 20 mg on a mg/m^2 basis. Fertility studies, in which sumatriptan was administered by the intranasal route, were not conducted.

Pregnancy

Pregnancy Category C. In reproductive toxicity studies in rats and rabbits, oral treatment with sumatriptan was associated with embryolethality, fetal abnormalities, and pup mortality. When administered by the intravenous route to rabbits, sumatriptan has been shown to be embryolethal. Reproductive toxicity studies for sumatriptan by the intranasal route have not been conducted.

There are no adequate and well-controlled studies in pregnant women. Therefore, Sumatriptan Nasal Spray should be used during pregnancy only if the potential benefit justifies the potential risk to the fetus. In assessing this information, the following findings should be considered.

Embryolethality: When given orally or intravenously to pregnant rabbits daily throughout the period of organogenesis, sumatriptan caused embryolethality at doses at or close to those producing maternal toxicity. In the oral studies this dose was 100 mg/kg/day, and in the intravenous studies this dose was 2.0 mg/kg/day. The mechanism of the embryolethality is not known. The highest no-effect dose for embryolethality by the oral route was 50 mg/kg/day, which is approximately 48 times the maximum single recommended human intranasal dose of 20 mg on a mg/m^2 basis. By the intravenous route, the highest no-effect dose was 0.75 mg/kg/day, or approximately 0.7 times the maximum single recommended human intranasal dose of 20 mg on a mg/m^2 basis.

The intravenous administration of sumatriptan to pregnant rats throughout organogenesis at 12.5 mg/kg/day, the maximum dose tested, did not cause embryolethality. This dose is approximately 6 times the maximum single recommended human intranasal dose of 20 mg on a mg/m^2 basis. Additionally, in a study in rats given subcutaneous sumatriptan daily, prior to and throughout pregnancy, at 60 mg/kg/day, the maximum dose tested, there was no evidence of increased embryo/fetal lethality. This dose is equivalent to approximately 29 times the maximum recommended single human intranasal dose of 20 mg on a mg/m^2 basis.

Teratogenicity: Oral treatment of pregnant rats with sumatriptan during the period of organogenesis resulted in an increased incidence of blood vessel abnormalities (cervicothoracic and umbilical) at doses of approximately 250 mg/kg/day or higher. The highest no-effect dose was approximately 60 mg/kg/day, which is approximately 29 times the maximum single recommended human intranasal dose of 20 mg on a mg/m^2 basis. Oral treatment of pregnant rabbits with sumatriptan during the period of organogenesis resulted in an increased incidence of cervicothoracic vascular and skeletal abnormalities. The highest no-effect dose for these effects was 15 mg/kg/day, or approximately 14 times the maximum single recommended human intranasal dose of 20 mg on a mg/m^2 basis.

A study in which rats were dosed daily with oral sumatriptan prior to and throughout gestation demonstrated embryo/fetal toxicity (decreased body weight, decreased ossification, increased incidence of rib variations) and an increased incidence of a syndrome of malformations (short tail/short body and vertebral disorganization) at 500 mg/kg/day. The highest no-effect dose was 50 mg/kg/day, or approximately 24 times the maximum single recommended human intranasal dose of 20 mg on a mg/m^2 basis. In a study in rats dosed daily with subcutaneous sumatriptan prior to and throughout pregnancy, at a dose of 60 mg/kg/day, the maximum dose tested, there was no evidence of teratogenicity. This dose is equivalent to approximately 29 times the maximum recommended single human intranasal dose of 20 mg on a mg/m^2 basis.

Pup Deaths: Oral treatment of pregnant rats with sumatriptan during the period of organogenesis resulted in a decrease in pup survival between birth and postnatal day 4 at doses of approximately 250 mg/kg/day or higher. The highest no-effect dose for this effect was approximately 60 mg/kg/day, or 29 times the maximum single recommended human intranasal dose of 20 mg on a mg/m^2 basis.

Oral treatment of pregnant rats with sumatriptan from gestational day 17 through postnatal day 21 demonstrated a decrease in pup survival measured at postnatal days 2, 4, and 20 at the dose of 1,000 mg/kg/day. The highest no-effect dose for this finding was 100 mg/kg/day, approximately 49 times the maximum single recommended human intranasal dose of 20 mg on a mg/m^2 basis. In a similar study in rats by the subcutaneous route there was no increase in pup death at 81 mg/kg/day, the highest dose tested, which is equivalent to 40 times the maximum single recommended human intranasal dose of 20 mg on a mg/m^2 basis.

Nursing Mothers

Sumatriptan is excreted in human breast milk following subcutaneous administration. Infant exposure to sumatriptan can be minimized by avoiding breastfeeding for 12 hours after treatment with Sumatriptan Nasal Spray.

Pediatric Use

Safety and effectiveness of sumatriptan in pediatric patients under 18 years of age have not been established; therefore, Sumatriptan Nasal Spray is not recommended for use in patients under 18 years of age.

Two controlled clinical trials evaluated sumatriptan nasal spray (5 to 20 mg) in 1,248 adolescent migraineurs aged 12 to 17 years who treated a single attack. The studies did not establish the efficacy of sumatriptan nasal spray compared with placebo in the treatment of migraine in adolescents. Adverse events observed in these clinical trials were similar in nature to those reported in clinical trials in adults.

Five controlled clinical trials (2 single attack studies, 3 multiple attack studies) evaluating oral sumatriptan (25 to 100 mg) in pediatric patients aged 12 to 17 years enrolled a total of 701 adolescent migraineurs. These studies did not establish the efficacy of oral sumatriptan compared with placebo in the treatment of migraine in adolescents. Adverse events observed in these clinical trials were similar in nature to those reported in clinical trials in adults. The frequency of all adverse events in these patients appeared to be both dose- and age-dependent, with younger patients reporting events more commonly than older adolescents.

Postmarketing experience documents that serious adverse events have occurred in the pediatric population after use of subcutaneous, oral, and/or intranasal sumatriptan. These reports include events similar in nature to those reported rarely in adults, including stroke, visual loss, and death. A myocardial infarction has been reported in a 14-year-old male following the use of oral sumatriptan; clinical signs occurred within 1 day of drug administration. Since clinical data to determine the frequency of serious adverse events in pediatric patients who might receive injectable, oral, or intranasal sumatriptan are not presently available, the use of sumatriptan in patients aged younger than 18 years is not recommended.

Geriatric Use

The use of sumatriptan in elderly patients is not recommended because elderly patients are more likely to have decreased hepatic function, they are at higher risk for CAD, and blood pressure increases may be more pronounced in the elderly (see WARNINGS).

ADVERSE REACTIONS

Serious cardiac events, including some that have been fatal, have occurred following the use of sumatriptan injection or tablets. These events are extremely rare and most have been reported in patients with risk factors predictive of CAD. Events reported have included coronary artery vasospasm, transient myocardial ischemia, myocardial infarction, ventricular tachycardia, and ventricular fibrillation (see CONTRAINDICATIONS, WARNINGS, and PRECAUTIONS).

Significant hypertensive episodes, including hypertensive crises, have been reported on rare occasions in patients with or without a history of hypertension (see WARNINGS).

Incidence in Controlled Clinical Trials

Among 3,653 patients treated with sumatriptan nasal spray in active- and placebo-controlled clinical trials, less than 0.4% of patients withdrew for reasons related to adverse events. Table 2 lists adverse events that occurred in worldwide placebo-controlled clinical trials in 3,419 migraineurs. The events cited reflect experience gained under closely monitored conditions of clinical trials in a highly selected patient population. In actual clinical practice or in other clinical trials, these frequency estimates may not apply, as the conditions of use, reporting behavior, and the kinds of patients treated may differ.

Only events that occurred at a frequency of 1% or more in the sumatriptan nasal spray 20-mg treatment group and were more frequent in that group than in the placebo group are included in Table 2.

Table 2. Treatment-Emergent Adverse Events Reported by at Least 1% of Patients in Controlled Migraine Trials
Adverse Event Type | Percent of Patients Reporting
Adverse Event Type | Placebo (n = 704) | Sumatriptan 5 mg (n = 496) | Sumatriptan 10 mg (n = 1,007) | Sumatriptan 20 mg (n = 1,212)
Atypical sensations
Burning sensation | 0.1% | 0.4% | 0.6% | 1.4%
Ear, nose, and throat
Disorder/discomfort of nasal cavity/sinuses | 2.4% | 2.8% | 2.5% | 3.8%
Throat discomfort | 0.9% | 0.8% | 1.8% | 2.4%
Gastrointestinal
Nausea and/or vomiting | 11.3% | 12.2% | 11.0% | 13.5%
Neurological
Bad/unusual taste | 1.7% | 13.5% | 19.3% | 24.5%
Dizziness/vertigo | 0.9% | 1.0% | 1.7% | 1.4%

Phonophobia also occurred in more than 1% of patients but was more frequent on placebo.

Sumatriptan nasal spray is generally well tolerated. Across all doses, most adverse reactions were mild and transient and did not lead to long-lasting effects. The incidence of adverse events in controlled clinical trials was not affected by gender, weight, or age of the patients; use of prophylactic medications; or presence of aura. There were insufficient data to assess the impact of race on the incidence of adverse events.

Other Events Observed in Association With the Administration of Sumatriptan Nasal Spray

In the paragraphs that follow, the frequencies of less commonly reported adverse clinical events are presented. Because the reports include events observed in open and uncontrolled studies, the role of sumatriptan nasal spray in their causation cannot be reliably determined. Furthermore, variability associated with adverse event reporting, the terminology used to describe adverse events, etc., limit the value of the quantitative frequency estimates provided.

Event frequencies are calculated as the number of patients who used sumatriptan nasal spray (5, 10, or 20 mg in controlled and uncontrolled trials) and reported an event divided by the total number of patients (N = 3,711) exposed to sumatriptan nasal spray. All reported events are included except those already listed in the previous table, those too general to be informative, and those not reasonably associated with the use of the drug. Events are further classified within body system categories and enumerated in order of decreasing frequency using the following definitions: infrequent adverse events are those occurring in 1/100 to 1/1,000 patients and rare adverse events are those occurring in fewer than 1/1,000 patients.

Atypical Sensations: Infrequent were tingling, warm/hot sensation, numbness, pressure sensation, feeling strange, feeling of heaviness, feeling of tightness, paresthesia, cold sensation, and tight feeling in head. Rare were dysesthesia and prickling sensation.

Cardiovascular: Infrequent were flushing and hypertension (see WARNINGS), palpitations, tachycardia, changes in ECG, and arrhythmia (see WARNINGS and PRECAUTIONS). Rare were abdominal aortic aneurysm, hypotension, bradycardia, pallor, and phlebitis.

Chest Symptoms: Infrequent were chest tightness, chest discomfort, and chest pressure/heaviness (see PRECAUTIONS: General).

Ear, Nose, and Throat: Infrequent were disturbance of hearing and ear infection. Rare were otalgia and Meniere disease.

Endocrine and Metabolic: Infrequent was thirst. Rare were galactorrhea, hypothyroidism, and weight loss.

Eye: Infrequent were irritation of eyes and visual disturbance.

Gastrointestinal: Infrequent were abdominal discomfort, diarrhea, dysphagia, and gastroesophageal reflux. Rare were constipation, flatulence/eructation, hematemesis, intestinal obstruction, melena, gastroenteritis, colitis, hemorrhage of gastrointestinal tract, and pancreatitis.

Mouth and Teeth: Infrequent was disorder of mouth and tongue (e.g., burning of tongue, numbness of tongue, dry mouth).

Musculoskeletal: Infrequent were neck pain/stiffness, backache, weakness, joint symptoms, arthritis, and myalgia. Rare were muscle cramps, tetany, intervertebral disc disorder, and muscle stiffness.

Neurological: Infrequent were drowsiness/sedation, anxiety, sleep disturbances, tremors, syncope, shivers, chills, depression, agitation, sensation of lightness, and mental confusion. Rare were difficulty concentrating, hunger, lacrimation, memory disturbances, monoplegia/diplegia, apathy, disturbance of smell, disturbance of emotions, dysarthria, facial pain, intoxication, stress, decreased appetite, difficulty coordinating, euphoria, and neoplasm of pituitary.

Respiratory: Infrequent were dyspnea and lower respiratory tract infection. Rare was asthma.

Skin: Infrequent were rash/skin eruption, pruritus, and erythema. Rare were herpes, swelling of face, sweating, and peeling of skin.

Urogenital: Infrequent were dysuria, disorder of breasts, and dysmenorrhea. Rare were endometriosis and increased urination.

Miscellaneous: Infrequent were cough, edema, and fever. Rare were hypersensitivity, swelling of extremities, voice disturbances, difficulty in walking, and lymphadenopathy.

Other Events Observed in the Clinical Development of Sumatriptan

The following adverse events occurred in clinical trials with sumatriptan injection and sumatriptan tablets. Because the reports include events observed in open and uncontrolled studies, the role of sumatriptan in their causation cannot be reliably determined. All reported events are included except those already listed, those too general to be informative, and those not reasonably associated with the use of the drug.

Breasts: Breast swelling; cysts, lumps, and masses of breasts; nipple discharge; primary malignant breast neoplasm; and tenderness.

Cardiovascular: Abnormal pulse, angina, atherosclerosis, cerebral ischemia, cerebrovascular lesion, heart block, peripheral cyanosis, pulsating sensations, Raynaud syndrome, thrombosis, transient myocardial ischemia, various transient ECG changes (nonspecific ST or T wave changes, prolongation of PR or QTc intervals, sinus arrhythmia, nonsustained ventricular premature beats, isolated junctional ectopic beats, atrial ectopic beats, delayed activation of the right ventricle), and vasodilation.

Ear, Nose, and Throat: Allergic rhinitis; ear, nose, and throat hemorrhage; external otitis; feeling of fullness in the ear(s); hearing disturbances; hearing loss; nasal inflammation; sensitivity to noise; sinusitis; tinnitus; and upper respiratory inflammation.

Endocrine and Metabolic: Dehydration; endocrine cysts, lumps, and masses; elevated thyrotropin stimulating hormone (TSH) levels; fluid disturbances; hyperglycemia; hypoglycemia; polydipsia; and weight gain.

Eye: Accommodation disorders, blindness and low vision, conjunctivitis, disorders of sclera, external ocular muscle disorders, eye edema and swelling, eye itching, eye hemorrhage, eye pain, keratitis, mydriasis, and vision alterations.

Gastrointestinal: Abdominal distention, dental pain, disturbances of liver function tests, dyspeptic symptoms, feelings of gastrointestinal pressure, gallstones, gastric symptoms, gastritis, gastrointestinal pain, hypersalivation, hyposalivation, oral itching and irritation, peptic ulcer, retching, salivary gland swelling, and swallowing disorders.

Hematological Disorders: Anemia.

Injection Site Reaction

Miscellaneous: Contusions, fluid retention, hematoma, hypersensitivity to various agents, jaw discomfort, miscellaneous laboratory abnormalities, overdose, “serotonin agonist effect,” and speech disturbance.

Musculoskeletal: Acquired musculoskeletal deformity, arthralgia and articular rheumatitis, muscle atrophy, muscle tiredness, musculoskeletal inflammation, need to flex calf muscles, rigidity, tightness, and various joint disturbances (pain, stiffness, swelling, ache).

Neurological: Aggressiveness, bradylogia, cluster headache, convulsions, detachment, disturbances of taste, drug abuse, dystonia, facial paralysis, globus hystericus, hallucinations, headache, heat sensitivity, hyperesthesia, hysteria, increased alertness, malaise/fatigue, migraine, motor dysfunction, myoclonia, neuralgia, neurotic disorders, paralysis, personality change, phobia, photophobia, psychomotor disorders, radiculopathy, raised intracranial pressure, relaxation, stinging sensations, transient hemiplegia, simultaneous hot and cold sensations, suicide, tickling sensations, twitching, and yawning.

Pain and Other Pressure Sensations: Chest pain, neck tightness/pressure, throat/jaw pain/tightness/pressure, and pain (location specified).

Respiratory: Breathing disorders, bronchitis, diseases of the lower respiratory tract, hiccoughs, and influenza.

Skin: Dry/scaly skin, eczema, seborrheic dermatitis, skin nodules, skin tenderness, tightness of skin, and wrinkling of skin.

Urogenital: Abortion, abnormal menstrual cycle, bladder inflammation, hematuria, inflammation of fallopian tubes, intermenstrual bleeding, menstruation symptoms, micturition disorders, renal calculus, urethritis, urinary frequency, and urinary infections.

Postmarketing Experience (Reports for Subcutaneous or Oral Sumatriptan)

The following section enumerates potentially important adverse events that have occurred in clinical practice and that have been reported spontaneously to various surveillance systems. The events enumerated represent reports arising from both domestic and nondomestic use of oral or subcutaneous dosage forms of sumatriptan. The events enumerated include all except those already listed in the ADVERSE REACTIONS section above or those too general to be informative. Because the reports cite events reported spontaneously from worldwide postmarketing experience, frequency of events and the role of sumatriptan in their causation cannot be reliably determined. It is assumed, however, that systemic reactions following sumatriptan use are likely to be similar regardless of route of administration.

Blood: Hemolytic anemia, pancytopenia, thrombocytopenia.

Cardiovascular: Atrial fibrillation, cardiomyopathy, colonic ischemia (see WARNINGS), Prinzmetal variant angina, pulmonary embolism, shock, thrombophlebitis.

Ear, Nose, and Throat: Deafness.

Eye: Ischemic optic neuropathy, retinal artery occlusion, retinal vein thrombosis, loss of vision.

Gastrointestinal: Ischemic colitis with rectal bleeding (see WARNINGS), xerostomia.

Hepatic: Elevated liver function tests.

Neurological: Central nervous system vasculitis, cerebrovascular accident, dysphasia, serotonin syndrome, subarachnoid hemorrhage.

Non-Site Specific: Angioneurotic edema, cyanosis, death (see WARNINGS), temporal arteritis.

Psychiatry: Panic disorder.

Respiratory: Bronchospasm in patients with and without a history of asthma.

Skin: Exacerbation of sunburn, hypersensitivity reactions (allergic vasculitis, erythema, pruritus, rash, shortness of breath, urticaria; in addition, severe anaphylaxis/anaphylactoid reactions have been reported [see WARNINGS]), photosensitivity.

Urogenital: Acute renal failure.

DRUG ABUSE AND DEPENDENCE

One clinical study with sumatriptan injection enrolling 12 patients with a history of substance abuse failed to induce subjective behavior and/or physiologic response ordinarily associated with drugs that have an established potential for abuse.

OVERDOSAGE

In clinical trials, the highest single doses of sumatriptan nasal spray administered without significant adverse effects were 40 mg to 12 volunteers and 40 mg to 85 migraine patients, which is twice the highest single recommended dose. In addition, 12 volunteers were administered a total daily dose of 60 mg (20 mg 3 times daily) for 3.5 days without significant adverse events.

Overdose in animals has been fatal and has been heralded by convulsions, tremor, paralysis, inactivity, ptosis, erythema of the extremities, abnormal respiration, cyanosis, ataxia, mydriasis, salivation, and lacrimation. The elimination half-life of sumatriptan is about 2 hours (see CLINICAL PHARMACOLOGY), and therefore monitoring of patients after overdose with Sumatriptan Nasal Spray should continue for at least 10 hours or while symptoms or signs persist. It is unknown what effect hemodialysis or peritoneal dialysis has on the serum concentrations of sumatriptan.

DOSAGE AND ADMINISTRATION

In controlled clinical trials, single doses of 5, 10, or 20 mg of sumatriptan nasal spray administered into 1 nostril were effective for the acute treatment of migraine in adults. A greater proportion of patients had headache response following a 20-mg dose than following a 5- or 10-mg dose (see CLINICAL TRIALS). Individuals may vary in response to doses of Sumatriptan Nasal Spray. The choice of dose should therefore be made on an individual basis, weighing the possible benefit of the 20-mg dose with the potential for a greater risk of adverse events. A 10-mg dose may be achieved by the administration of a single 5-mg dose in each nostril. There is evidence that doses above 20 mg do not provide a greater effect than 20 mg.

If the headache returns, the dose may be repeated once after 2 hours, not to exceed a total daily dose of 40 mg. The safety of treating an average of more than 4 headaches in a 30-day period has not been established.

HOW SUPPLIED

Sumatriptan Nasal Spray 20 mg (NDC 54868-6052-0) are each supplied in boxes of 6 nasal spray devices. Each unit dose spray supplies 20 mg, respectively, of sumatriptan.

Store between 36° and 86°F (2° and 30°C). Protect from light.

ANIMAL TOXICOLOGY

Corneal Opacities

Dogs receiving oral sumatriptan developed corneal opacities and defects in the corneal epithelium. Corneal opacities were seen at the lowest dosage tested, 2 mg/kg/day, and were present after 1 month of treatment. Defects in the corneal epithelium were noted in a 60-week study. Earlier examinations for these toxicities were not conducted and no-effect doses were not established; however, the relative exposure at the lowest dose tested was approximately 5 times the human exposure after a 100-mg oral dose or 3 times the human exposure after a 6-mg subcutaneous dose or 22 times the human exposure after a single 20-mg intranasal dose. There is evidence of alterations in corneal appearance on the first day of intranasal dosing to dogs. Changes were noted at the lowest dose tested, which was approximately 2 times the maximum single human intranasal dose of 20 mg on a mg/m^2 basis.

Manufactured by

GlaxoSmithKline Manufacturing S.p.A.

for Sandoz Inc.

Princeton, NJ 08540

February 2010

SNS-SZ:2PI

PATIENT INFORMATION

The following wording is contained in a separate leaflet provided for patients.

Information for the Patient

Sumatriptan Nasal Spray

Read this leaflet carefully before you start to take Sumatriptan Nasal Spray. Keep the leaflet for reference because it gives you a summary of important information about Sumatriptan Nasal Spray.

Read the leaflet that comes with each refill of your prescription because there may be new information.

This leaflet does not have all the information about Sumatriptan Nasal Spray. Ask your healthcare provider for more information or advice.

What is Sumatriptan Nasal Spray?

Sumatriptan Nasal Spray is a kind of medicine called a triptan. You should take it only if you have a prescription.

Sumatriptan Nasal Spray is used to relieve your migraine. It is not used to prevent attacks or reduce the number of attacks you have. Use Sumatriptan Nasal Spray only to treat an actual migraine attack.

The decision to use Sumatriptan Nasal Spray is one that you and your healthcare provider should make together, based on your personal needs and health.

Talk with your healthcare provider before taking Sumatriptan Nasal Spray

1. Risk factors for heart disease to tell your healthcare provider:

Tell your healthcare provider if you have risk factors for heart disease such as:

- high blood pressure
- high cholesterol
- being overweight
- diabetes
- smoking
- strong family history of heart disease
- you are postmenopausal
- you are a male over 40 years of age

If you do have risk factors for heart disease, your healthcare provider should check you for heart disease to see if Sumatriptan Nasal Spray is right for you.

Although most of the people who have taken sumatriptan have not had any serious side effects, some have had serious heart problems. Deaths have been reported, but these were rare considering the extensive worldwide use of sumatriptan . Usually, serious problems happened in people with known heart disease. It was not clear whether sumatriptan had anything to do with these deaths.

2. Important questions to ask yourself before you take Sumatriptan Nasal Spray:

If the answer to any of the following questions is YES or if you do not know the answer, then please talk with your healthcare provider before you take Sumatriptan Nasal Spray.

- Are you pregnant? Do you think you might be pregnant? Are you trying to become pregnant? Are you not using adequate contraception? Are you breastfeeding?
- Do you have any chest pain, heart disease, shortness of breath, or irregular heartbeats? Have you had a heart attack?
- Do you have risk factors for heart disease (see list above)?
- Have you had a stroke, a mini-stroke (also called a transient ischemic attack or TIA), or Raynaud syndrome?
- Do you have high blood pressure?
- Have you ever had to stop taking this or any other medicine because of an allergy or other problems?
- Are you taking any other migraine medicines, including other triptans? Are you taking any medicines containing ergotamine, dihydroergotamine, or methysergide?
- Are you taking any medicine for depression or other health problems such as a monoamine oxidase inhibitor, selective serotonin reuptake inhibitor (SSRI), or serotonin norepinephrine reuptake inhibitor (SNRI)? Common SSRIs are citalopram HBr (CELEXA®), escitalopram oxalate (LEXAPRO®), paroxetine (PAXIL®), fluoxetine (PROZAC®/SARAFEM®), olanzapine/fluoxetine (SYMBYAX®), sertraline (ZOLOFT®), and fluvoxamine. Common SNRIs are duloxetine (CYMBALTA®) and venlafaxine (EFFEXOR®).
- Have you had, or do you have, any disease of the liver or kidney?
- Have you had, or do you have, epilepsy or seizures?
- Is this headache different from your usual migraine attacks?

Remember, if you answered YES to any of the above questions, then talk with your healthcare provider about it.

Important points about Sumatriptan Nasal Spray

1. The use of Sumatriptan Nasal Spray during pregnancy:

Do not take Sumatriptan Nasal Spray if you are pregnant, think you might be pregnant, are trying to become pregnant, or are not using adequate contraception unless you have talked with your healthcare provider about this.

2. How to take Sumatriptan Nasal Spray:

Before taking Sumatriptan Nasal Spray, see the enclosed instructions leaflet.

For adults, the usual dose is a single nasal spray in 1 nostril. If your headache comes back, you can take a second nasal spray anytime after 2 hours after you took the first spray.

For any attack where you have no response to the first nasal spray, do not take a second nasal spray without first talking with your healthcare provider. Do not take more than a total of 40 mg of Sumatriptan Nasal Spray in any 24-hour period. The safety of treating an average of more than 4 headaches in a 30-day period has not been established.

The effects of long-term repeated use of sumatriptan nasal spray on the surfaces of the nose and throat have not been specifically studied.

3. Caution for activities requiring alertness:

You may feel drowsy or dizzy because of your migraine or treatment with Sumatriptan Nasal Spray. Use caution for activities requiring alertness (like driving or using machines).

4. What to do if you take an overdose:

If you have taken more medicine than has been prescribed for you, contact either your healthcare provider, hospital emergency department, or nearest poison control center right away.

5. How to store your medicine:

Keep your medicine in a safe place where children cannot reach it. It may be harmful to children.

Store your medicine away from heat and light. Do not store at temperatures above 86°F (30°C) or below 36°F (2°C).

The expiration date of your medicine is printed on the packaging. If your medicine has expired, throw it away.

If your healthcare provider decides to stop your treatment, do not keep any leftover medicine unless your healthcare provider tells you to.

Some possible side effects of Sumatriptan Nasal Spray

- Some patients feel pain or tightness in the chest or throat when using Sumatriptan Nasal Spray. If this happens to you, tell your healthcare provider before taking any more Sumatriptan Nasal Spray. If the chest pain, tightness, or pressure is severe or does not go away, call your healthcare provider right away.
- Call your healthcare provider right away if you have sudden and/or severe abdominal pain after you take Sumatriptan Nasal Spray.
- Some people may have a reaction called serotonin syndrome when they take certain kinds of medicines for depression called SSRIs or SNRIs while they are taking Sumatriptan Nasal Spray. Symptoms may include confusion, hallucinations, fast heartbeat, feeling faint, fever, sweating, muscle spasm, difficulty walking, and/or diarrhea. Call your healthcare provider right away if you have any of these symptoms after taking Sumatriptan Nasal Spray.
- Shortness of breath; wheeziness; heart throbbing; swelling of eyelids, face, or lips; or a skin rash, skin lumps, or hives happens rarely. If it happens to you, then tell your healthcare provider right away. Do not take any more Sumatriptan Nasal Spray unless your healthcare provider tells you to.
- Some people may feel tingling, heat, flushing (redness of face lasting a short time), heaviness, or pressure after taking Sumatriptan Nasal Spray. A few people may feel drowsy, dizzy, tired, sick, or may experience nasal irritation. If you have any of these symptoms, tell your healthcare provider at your next visit.
- If you feel unwell in any other way or have any symptoms that you do not understand, you should contact your healthcare provider right away.

The following are registered trademarks of their respective owners: CELEXA, LEXAPRO/Forest Laboratories, Inc.; PAXIL/GlaxoSmithKline; PROZAC, SARAFEM, SYMBYAX, CYMBALTA/Eli Lilly and Company; ZOLOFT/Pfizer Inc.; EFFEXOR/Wyeth Corporation.

Manufactured by

GlaxoSmithKline Manufacturing S.p.A.

for Sandoz Inc.

Princeton, NJ 08540

February 2010

SNS-SZ:2PIL

Additional barcode label applied by:
Physicians Total Care, Inc.
Tulsa, Oklahoma 74146

Principal Display Panel

NDC 54868-6052-0

Sumatriptan Nasal Spray

20 mg

Each unit dose spray contains 20 mg of sumatriptan.

1 Spray per unit. Do not test before use.

See package insert for full prescribing information.

Store between 36o and 86oF (2o and 30oC).

Protect from light.

Rx only